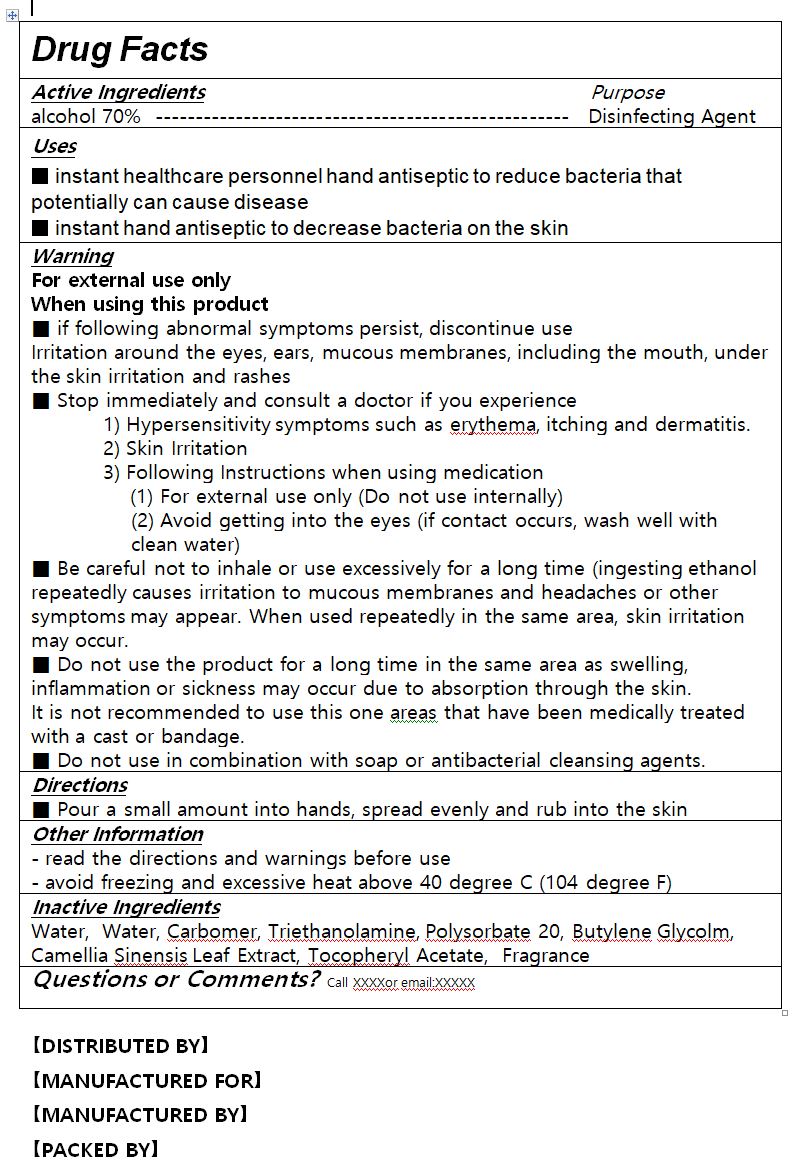 DRUG LABEL: Canpaco Hand Sanitizer
NDC: 76586-108 | Form: GEL
Manufacturer: HEALKINBIO CO.
Category: otc | Type: HUMAN OTC DRUG LABEL
Date: 20200611

ACTIVE INGREDIENTS: ALCOHOL 62 mL/100 mL
INACTIVE INGREDIENTS: WATER

Active Ingredient(s)

alcohol

Purpose

Purpose: Antiseptic

Use

 Hand sanitizing to help reduce bacteria on the skin

Warnings

 For external use only.
 Flammable, keep away from fire or flame.
 When using this product, avoid contact with the eyes. In case of contact, rinse eyes thoroughly with water.
 Stop use and ask a doctor if irritation or redness appears and lasts.

 Keep out of reach of children. If swallowed, get medical help or contact a Poison Control Center immediately.

Directions

 Take suitable amount of sanitizer in the hand. Wet thoroughly and rub hands together until dry

Other information

 Store in room temperature 0~30℃

 Period of Use: 36 Months after manufacturing date

 Manufacturing Date and No. Printed on bottle

INACTIVE INGREDIENT

Water, Carbomer, Triethanolamine, Polysorbate 20, Butylene Glycolm, Camellia Sinensis Leaf Extract, Tocopheryl Acetate, Fragrance